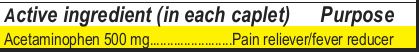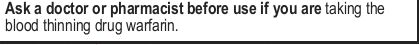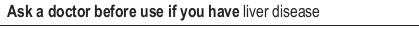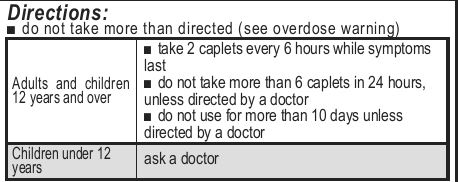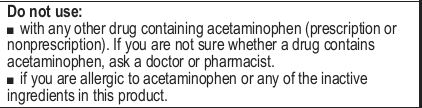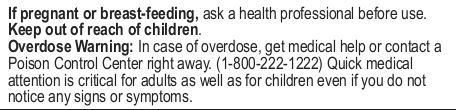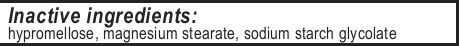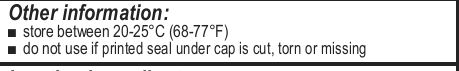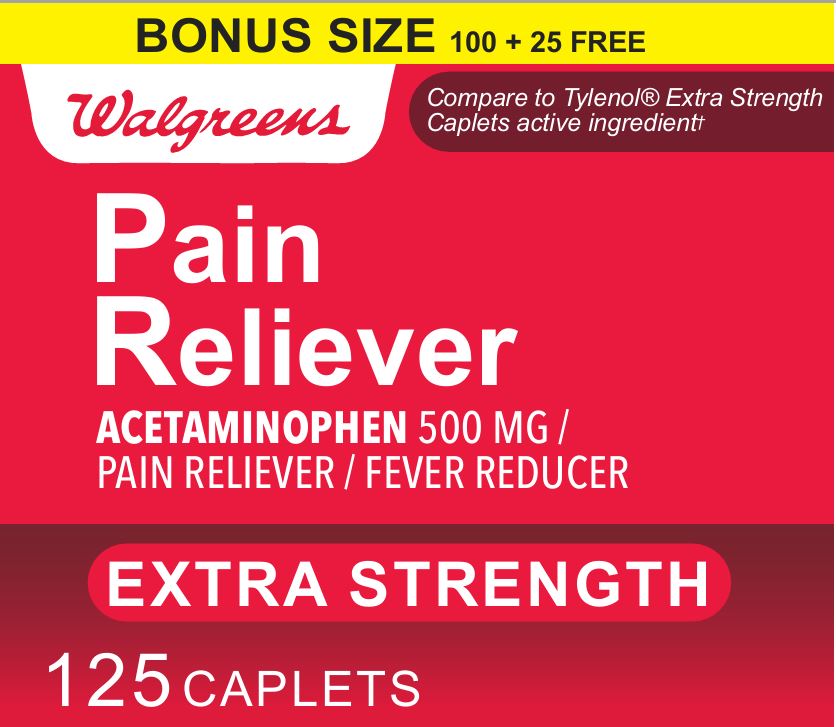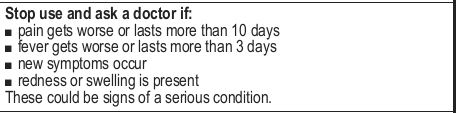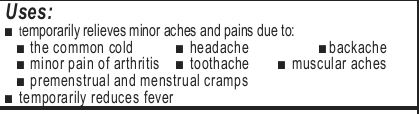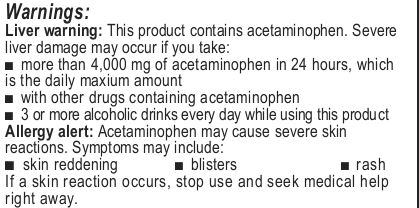 DRUG LABEL: Extra Strength Acetaminophen
NDC: 0363-6973 | Form: TABLET
Manufacturer: Walgreens Company
Category: otc | Type: HUMAN OTC DRUG LABEL
Date: 20221231

ACTIVE INGREDIENTS: ACETAMINOPHEN 500 mg/1 1
INACTIVE INGREDIENTS: SODIUM STARCH GLYCOLATE TYPE A POTATO; HYPROMELLOSE, UNSPECIFIED; MAGNESIUM STEARATE

Walgreens 125-Count Extra Strength

Questions or Comments? Call

Uses:
■ temporarily relieves minor aches and pains due to:
■ the common cold ■ headache ■backache
■ minor pain of arthritis ■ toothache ■ muscular aches
■ premenstrual and menstrual cramps
■ temporarily reduces fever